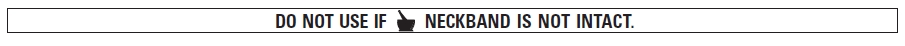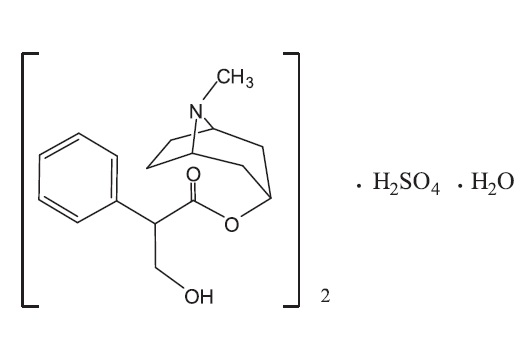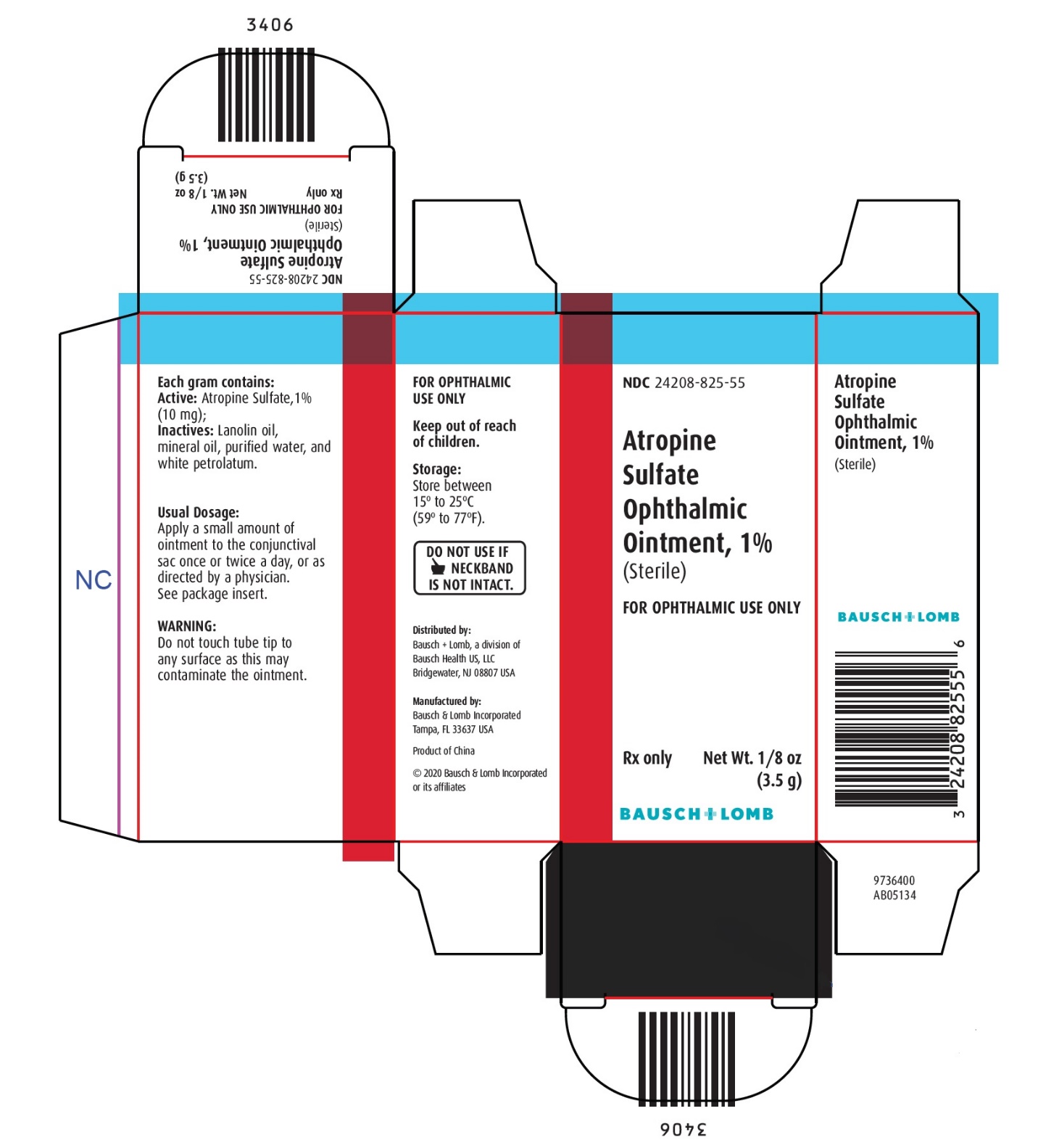 DRUG LABEL: Atropine Sulfate
NDC: 24208-825 | Form: OINTMENT
Manufacturer: Bausch & Lomb Incorporated
Category: prescription | Type: HUMAN PRESCRIPTION DRUG LABEL
Date: 20200402

ACTIVE INGREDIENTS: ATROPINE SULFATE 10 mg/1 g
INACTIVE INGREDIENTS: LANOLIN OIL; MINERAL OIL; WATER; PETROLATUM

Atropine Sulfate
Ophthalmic Ointment, 1% (Sterile)
Rx only

DESCRIPTION:

Atropine Sulfate Ophthalmic Ointment, 1% is a sterile topical anticholinergic for ophthalmic use. The active ingredient is represented by the chemical structural formula:

(C17H23NO3)2•H2SO4•H2O
Mol. Wt. 694.83

Chemical Name:

Benzeneacetic acid, α-(hydroxymethyl)-, 8-methyl-8-azabicyclo-[3.2.1]oct-3-yl ester, endo-(±)-, sulfate (2:1) (salt), monohydrate.

Each gram contains:

ACTIVE: Atropine Sulfate, 1% (10 mg); INACTIVES: Lanolin oil, mineral oil, purified water, and white petrolatum.

CHEMICAL PHARMACOLOGY

The anticholinergic effect of this product blocks the responses of the sphincter muscle of the iris and the accommodative muscle of the ciliary body to cholinergic stimulation, producing pupillary dilation (mydriasis) and paralysis of accommodation (cycloplegia).

INDICATIONS AND USAGE

For mydriasis and/or cycloplegia. For cycloplegic refraction, for pupillary dilation desired in inflammatory conditions of the iris and uveal tract.

CONTRAINDICATIONS

This product should not be used in patients with primary glaucoma or a predisposition to narrow anterior chamber angle glaucoma.

This product should not be used in pediatric patients who have previously had a severe systemic reaction to atropine. This product should not be used in those persons showing hypersensitivity to any component of this preparation.

WARNINGS

In pediatric patients, use with extreme caution. Excessive use in pediatric patients or in certain individuals with a previous history of susceptibility to belladonna alkaloids may produce systemic symptoms of atropine poisoning. If this occurs, discontinue medication and use appropriate therapy as outlined in OVERDOSAGE.

PRECAUTIONS

To avoid excessive systemic absorption, the lacrimal sac should be compressed by digital pressure for two to three minutes after instillation. To avoid inducing angle closure glaucoma, an estimation of the depth of the angle of the anterior chamber should be made. Administration of atropine in infants requires great caution.

Patient Warning:

Patients should be advised not to drive or engage in other hazardous activities while pupils are dilated. Patients may experience sensitivity to light and should protect eyes in bright illumination during dilation.

Parents should be warned not to get this preparation in their children’s mouth and to wash their own hands and the child’s hands following administration.

Carcinogenesis, Mutagenesis, Impairment of Fertility:

No studies have been conducted in animals or in humans to evaluate the potential of these effects.

Animal reproduction studies have not been performed with atropine. It is also not known whether atropine can cause fetal harm when administered to a pregnant woman or can affect reproduction capacity. Atropine should be given to pregnant women only if clearly needed.

Pediatric Use:

See CONTRAINDICATIONS and WARNINGS.

ADVERSE REACTIONS

Prolonged use may produce local irritation characterized by follicular conjunctivitis, vascular congestion, edema, exudate, and an eczematoid dermatitis. Severe reactions are manifested by hypotension with progressive respiratory depression. Coma and death have been reported in the very young.

To report SUSPECTED ADVERSE REACTIONS, contact Bausch & Lomb Incorporated at 1-800-321-4576 or FDA at 1-800-FDA-1088 or www.fda.gov/medwatch.

OVERDOSAGE

Systemic atropine toxicity is manifested by flushing and dryness of the skin (a rash may be present in pediatric patients), blurred vision, a rapid and irregular pulse, fever, abdominal distension in infants, mental aberration (hallucinosis) and loss of neuromuscular coordination.

Atropine poisoning, although distressing, is rarely fatal, even with large doses of atropine, and is self-limited if the cause is recognized and the atropine medication is discontinued. In severe intoxication, physostigmine salicylate may be administered parenterally to provide more prompt relief of the intoxication. Give physostigmine salicylate as 1-5 mL IV of dilution containing 1 mg in 5 mL of saline. The smaller dose is for pediatric patients, and injection should take not less than 2 minutes. EKG control is advisable. Dosage can be repeated every 5 minutes up to a total dose of 2 mg in pediatric patients and 6 mg in adults every 30 minutes. Physostigmine is contraindicated in hypotensive reactions. Atropine (1 mg) should be available for immediate injection if physostigmine causes bradycardia, convulsions or bronchoconstriction. In pediatric patients, the body surface must be kept moist.

Use extreme caution when employing short-acting barbiturates to control excitement.

DOSAGE AND ADMINISTRATION

Apply a small amount of ointment to the conjunctival sac once or twice a day, or as directed by a physician.

FOR OPHTHALMIC USE ONLY

HOW SUPPLIED

Atropine Sulfate Ophthalmic Ointment, 1% is supplied in an ophthalmic tip applicator tube in the following size:

3.5 g tubes - NDC 24208-825-55

STORAGE:

Store between 15° to 25°C (59° to 77°F).

Keep out of reach of children.

Distributed by:

Bausch + Lomb, a division of Bausch Health US, LLC
Bridgewater, NJ 08807 USA

Manufactured by:

Bausch & Lomb Incorporated, Tampa, FL 33637 USA

© 2020 Bausch & Lomb Incorporated or its affiliates

Rev. 04/2020

9115203 (Folded)
9115303 (Flat)

PACKAGE/LABEL PRINCIPAL DISPLAY PANEL

NDC 24208-825-55

Atropine

Sulfate

Ophthalmic

Ointment, 1%

(Sterile)

FOR OPHTALMIC USE ONLY

Rx only

Net. Wt. 1/8 oz. (3.5g)

BAUSCH + LOMB